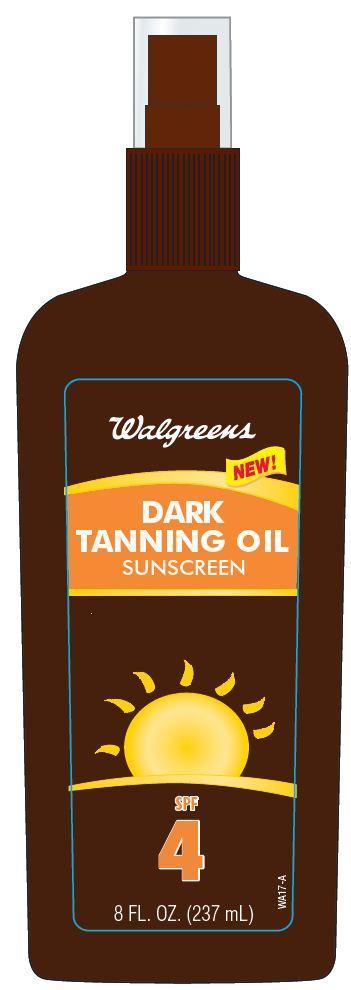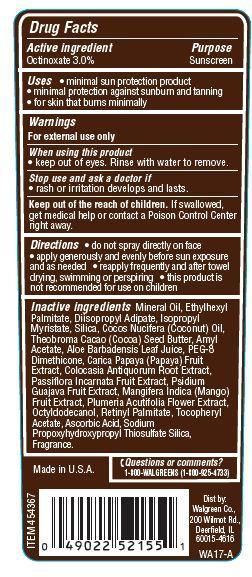 DRUG LABEL: Walgreens Dark Tanning Oil Sunscreen
NDC: 0363-4004 | Form: SPRAY
Manufacturer: WALGREEN CO.
Category: otc | Type: HUMAN OTC DRUG LABEL
Date: 20121204

ACTIVE INGREDIENTS: OCTINOXATE 3 g/100 g
INACTIVE INGREDIENTS: MINERAL OIL; ETHYLHEXYL PALMITATE; DIISOPROPYL ADIPATE; ISOPROPYL MYRISTATE; SILICON DIOXIDE; COCONUT OIL; AMYL ACETATE; PAPAYA; COLOCASIA ESCULENTA ROOT; .ALPHA.-TOCOPHEROL ACETATE; PASSIFLORA INCARNATA FRUIT; GUAVA; COCOA BUTTER; MANGO; PEG-8 DIMETHICONE; ALOE VERA LEAF; OCTYLDODECANOL; VITAMIN A PALMITATE; ASCORBIC ACID; PLUMERIA RUBRA FLOWER

Drug Facts

Active ingredient

Octinoxate 3.0%

Purpose

Sunscreen

Uses

- minimal sun protection product
- minimal protection against sunburn and tanning
- for skin that burns minimally

Warnings

For external use only

When using this product

- keep out of eyes. Rinse with water to remove

Stop use and ask a doctor if

- rash or irritation develops and lasts.

Keep Out of the reach of children.

If swallowed get medical help or contact a Poison Control Center right away.

Directions

- do not spray directly on face
- apply generously and evenly before sun exposure and as needed
- reapply frequently and after towel drying, swimming or perspiring.
- this product is not recommended for use on children

Inactive ingredients

Mineral Oil, Isopropyl Myristate, Sesamum Indicum (Sesame) Seed Oil, Persea Gratissima (Avocado) Oil, Amyl Acetate, Cocos Nucifera (Coconut) Oil, Squalane, Tocopheryl Acetate, Aloe Barbadensis Leaf Extract, Aleurites Moluccana Seed Extract, Carica Papaya (Papaya) Fruit Extract, Colocasia Antiquorum Root Extract, Mangifera Indica (Mango) Fruit Extract, Passiflora Incarnata Fruit Extract, Plumeria Acutifolia Flower Extract, Psidium Guajava Fruit Extract, Eucalyptus Globulus Leaf Oil, Fragrance.

Principal Display Panel

Walgreens
NEW
DARK
TANNING OIL
SUNSCREEN
SPF
4
8 FL. OZ. (237 mL)